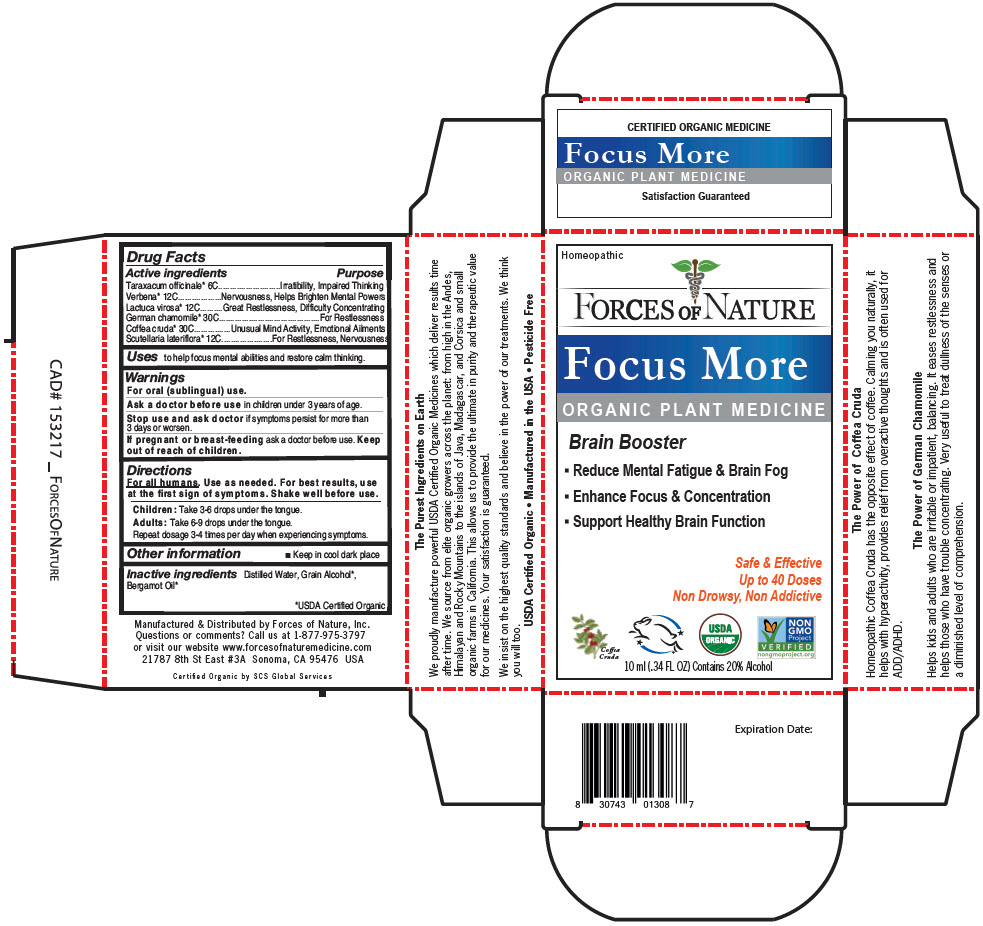 DRUG LABEL: More Focus
NDC: 51393-5003 | Form: SOLUTION/ DROPS
Manufacturer: Forces of Nature
Category: homeopathic | Type: HUMAN OTC DRUG LABEL
Date: 20210709

ACTIVE INGREDIENTS: TARAXACUM OFFICINALE ROOT 6 [hp_C]/100 mL; VERBENA HASTATA TOP 12 [hp_C]/100 mL; LACTUCA VIROSA LEAF 12 [hp_C]/100 mL; CHAMOMILE FLOWER OIL 30 [hp_C]/100 mL; ARABICA COFFEE BEAN 30 [hp_C]/100 mL; SCUTELLARIA LATERIFLORA  WHOLE 12 [hp_C]/100 mL
INACTIVE INGREDIENTS: Water; Alcohol; Bergamot Oil

More Focus

Drug Facts

ACTIVE INGREDIENT

Active ingredients | Purpose
Taraxacum officinale [USDA Certified Organic] 6C | Irratibility, Impaired Thinking
Verbena 12C | Nervousness, Helps Brighten Mental Powers
Lactuca virosa 12C | Great Restlessness, Difficulty Concentrating
German chamomile 30C | For Restlessness
Coffea cruda 30C | Unusual Mind Activity, Emotional Ailments
Scutellaria lateriflora 12C | For Restlessness, Nervousness

Uses

to help focus mental abilities and restore calm thinking.

Warnings

For oral (sublingual) use.

Ask a doctor before use in children under 3 years of age.

Stop use and ask doctor if symptoms persist for more than 3 days or worsen.

PREGNANCY OR BREAST FEEDING

If pregnant or breast-feeding ask a doctor before use.

Keep out of reach of children.

Directions

For all humans. Use as needed. For best results, use at the first sign of symptoms. Shake well before use.

Children

Take 3-6 drops under the tongue.

Adults

Take 6-9 drops under the tongue.

Repeat dosage 3-4 times per day when experiencing symptoms.

Other information

- Keep in cool dark place

Inactive ingredients

Distilled Water, Grain Alcohol, Bergamot Oil

Questions or comments?

Call us at 1-877-975-3797 or visit our website www.forcesofnaturemedicine.com

Manufactured & Distributed by Forces of Nature, Inc.
21787 8th St East # 3A Sonoma, CA 95476 USA

PRINCIPAL DISPLAY PANEL - 10 ml Bottle Carton

Homeopathic

FORCES OF NATURE

Focus More

ORGANIC PLANT MEDICINE

Brain Booster

- Reduce Mental Fatigue & Brain Fog
- Enhance Focus & Concentration
- Support Healthy Brain Function

Safe & Effective
Up to 40 Doses
Non Drowsy, Non Addictive

Coffea
Cruda

USDA
ORGANIC

NON
GMO
Project
VERIFIED
nongmoproject.org

10 ml (.34 FL OZ) Contains 20% Alcohol